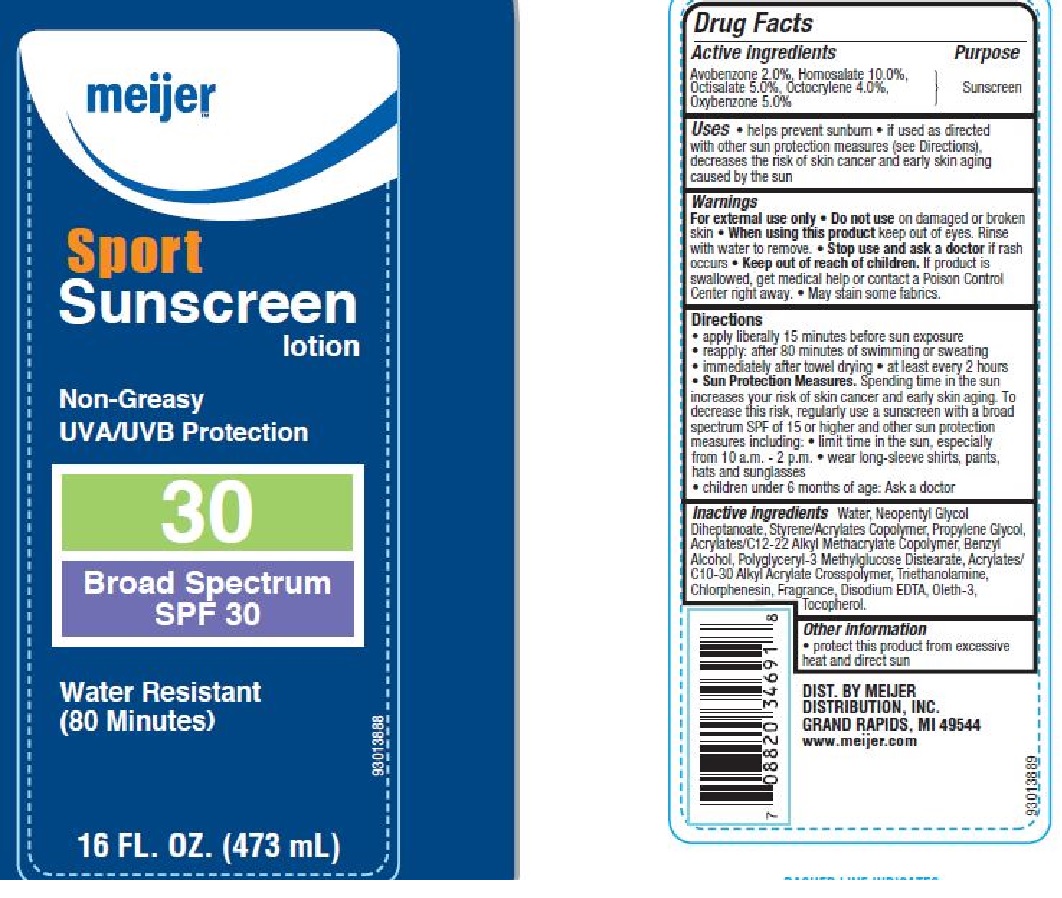 DRUG LABEL: Meijer Family Sport 30
NDC: 41250-389 | Form: LOTION
Manufacturer: Meijer
Category: otc | Type: HUMAN OTC DRUG LABEL
Date: 20160217

ACTIVE INGREDIENTS: AVOBENZONE 2 g/100 g; HOMOSALATE 10 g/100 g; OCTISALATE  5 g/100 g; OCTOCRYLENE 4 g/100 g; OXYBENZONE 5 g/100 g
INACTIVE INGREDIENTS: WATER; NEOPENTYL GLYCOL DIHEPTANOATE; PROPYLENE GLYCOL; BENZYL ALCOHOL; TROLAMINE; CHLORPHENESIN; EDETATE DISODIUM; OLETH-3; TOCOPHEROL

Drug Facts

Active Ingredients

AVOBENZONE 2.0%, HOMOSALATE 10.0%, OCTISALATE 5.0%, OCTOCRYLENE 4.0%,

OXYBENZONE 5.0%

Purpose

Sunscreen

Uses

- helps prevent sunburn
- if used as directed with other sun protection measures (See Directions), decreases the risk of skin cancer and early skin aging caused by the sun

Warning

For external use only

Do not use

on damaged or broken skin

When using this product

keep out of eyes. Rinse with water to remove.

Stop use and ask a doctor

if rash occurs

Keep out of reach of children.

If product is swallowed, get medical help or contact a Poison Control Center right away.

- May stain some fabrics.

Directions

- apply liberally15 minutes before sun exposure
- reapply: after 80 minutes of swimming or sweating
- immediately after towel drying
- at least every 2 hours
- Sun Protection Measures: Spending time in the sun increases your risk of skin cancer and early skin aging. To decrease this risk, regularly use a sunscreen with a broad spectrum SPF 15 or higher and other sun protection measures including:
- limit time in the sun, especially from 10 .am. to 2 p.m.
- wear long-sleeve shirts, pants, hats and sunglasses
- children under 6 months of age: Ask a doctor

Inactive Ingredients

Water, Neopentyl Glycol Diheptanoate, Styrene/Acrylates Copolymer, Propylene Glycol, Acrylates/C12-22 Alkyl Methacrylate Copolymer, Benzyl Alcohol, Polyglyceryl-3 Methylglucose Distearate, Acrylates/C10-30 Alkyl Acrylate Crosspolymer, Triethanolamine, Chlorphenesin, Fragrance, Disodium EDTA, Oleth-3, Tocopherol.

Other information

- protect this product from excessive heat and direct sun

Principle Display Label

NDC 41250-389-19

meijer

Sport Sunscreen lotion

Non- Greasy

UVA/UVB Protection

30

Broad Spectrum

SPF 30

Water Resistant

(80 Minutes)

16 FL. OZ. (473 mL)